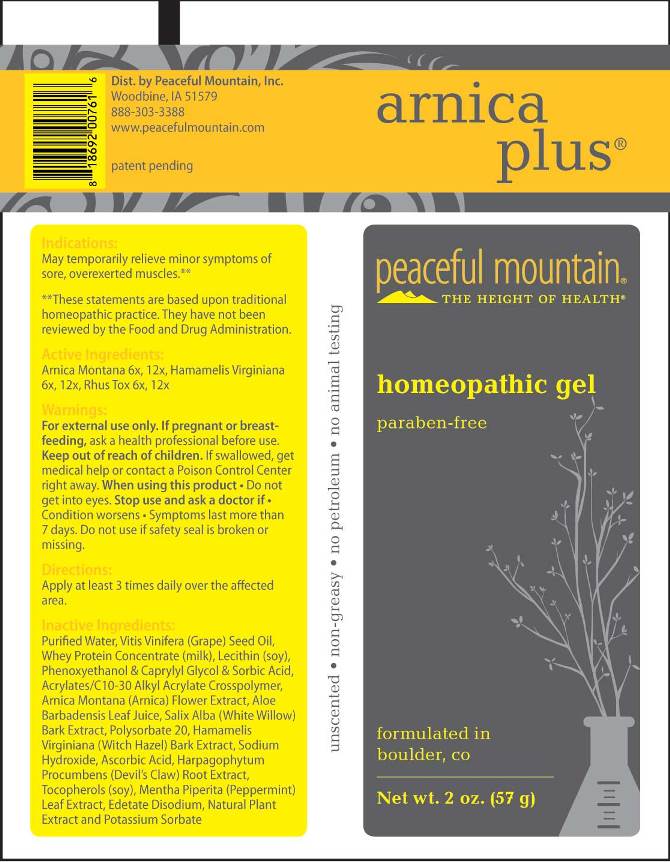 DRUG LABEL: Arnica Plus
NDC: 43846-0060 | Form: GEL
Manufacturer: Peaceful Mountain, Inc.
Category: homeopathic | Type: HUMAN OTC DRUG LABEL
Date: 20160929

ACTIVE INGREDIENTS: ARNICA MONTANA 6 [hp_X]/1 g; HAMAMELIS VIRGINIANA ROOT BARK/STEM BARK 6 [hp_X]/1 g; TOXICODENDRON PUBESCENS LEAF 6 [hp_X]/1 g
INACTIVE INGREDIENTS: WATER; GRAPE SEED OIL; WHEY; LECITHIN, SOYBEAN; SODIUM HYDROXIDE; PHENOXYETHANOL; CAPRYLYL GLYCOL; SORBIC ACID; CARBOMER INTERPOLYMER TYPE A (ALLYL SUCROSE CROSSLINKED); ARNICA MONTANA FLOWER; ALOE VERA LEAF; SALIX ALBA BARK; HAMAMELIS VIRGINIANA BARK; ASCORBIC ACID; HARPAGOPHYTUM PROCUMBENS ROOT; POLYSORBATE 20; TOCOPHEROL; MENTHA PIPERITA; EDETATE DISODIUM; OREGANO; POTASSIUM SORBATE

Drug Facts:

ACTIVE INGREDIENTS:

Arnica Montana 6X, 12X, Hamamelis Virginiana 6X, 12X, Rhus Tox 6X, 12X.

INDICATIONS:

May temporarily relieve minor symptoms of sore, overexerted muscles.**

**These statements are based upon traditional homeopathic practice. They have not been reviewed by the Food and Drug Administration.

WARNINGS:

For external use only. If pregnant or breast-feeding, ask a health professional before use.

Keep out of reach of children. If swallowed, get medical help or contact a Poison Control Center right away.

When using this product • Do not get into eyes. Stop use and ask a doctor if • Condition worsens • Symptoms last more than 7 days.

Do not use if safety seal is broken or missing.

Keep out of reach of children. If swallowed, get medical help or contact a Poison Control Center right away.

DIRECTIONS:

Apply at least 3 times daily over the affected area.

INDICATIONS:

May temporarily relieve minor symptoms of sore, overexerted muscles.**

**These statements are based upon traditional homeopathic practice. They have not been reviewed by the Food and Drug Administration.

INACTIVE INGREDIENTS:

Purified Water, Grapeseed (Seed) Carrier Oil, Whey Protein Concentrate, Lecithin (Soy) (Liquid)Sodium Hydroxide (Solution), Phenoxyethanol, Caprylyl Glycol, Sorbic Acid, Acrylates/C10-30 Alkyl Acrylate Crosspolymer (Carbopol (Ultrez 21), Arnica (flower), Aloe Barbadensis Leaf Juice, White Willow (bark), Witch Hazel (bark), Ascorbic Acid, Devil’s Claw (root), Polysorbate 20, Tocopherol [Vitamin E Oil], Peppermint (leaf), Edetate Disodium (EDTA), Natural plant extract (Origanox WS), Potassium Sorbate.

QUESTIONS:

Dist. By Peaceful Mountain, Inc.

Woodbine, IA 51579

888-303-3388

www.peacefulmountain.com

PACKAGE LABEL DISPLAY:

arnica

plus®

peaceful mountain

THE HEIGHT OF HEALTH

homeopathic gel

formulated in

boulder, co

Net wt. 2 oz. (57g)